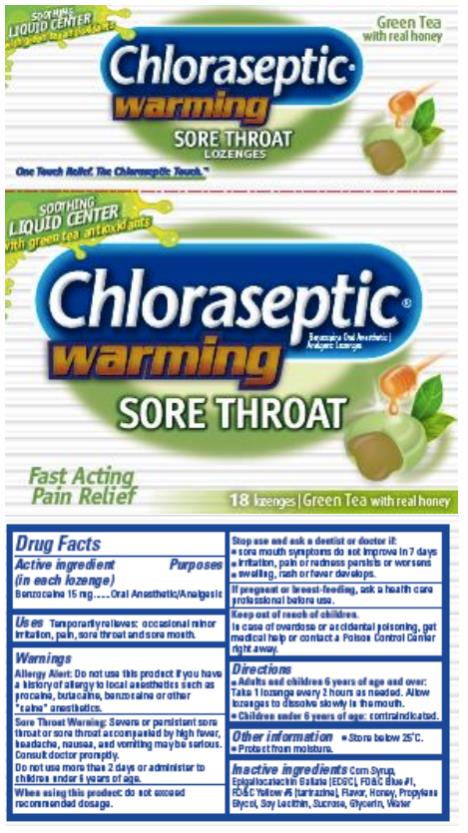 DRUG LABEL: Chloraseptic Warming Green Tea
NDC: 67172-020 | Form: LOZENGE
Manufacturer: Prestige Brands Holdings, Inc.
Category: otc | Type: HUMAN OTC DRUG LABEL
Date: 20230613

ACTIVE INGREDIENTS: BENZOCAINE 15 mg/1 1
INACTIVE INGREDIENTS: CORN SYRUP; EPIGALLOCATECHIN GALLATE; FD&C BLUE NO. 1; FD&C YELLOW NO. 5; HONEY; PROPYLENE GLYCOL; LECITHIN, SOYBEAN; SUCROSE; GLYCERIN; WATER

Chloraseptic Warming Green Tea Lozenge

Drug Facts

Active ingredient

(in each lozenge)

Benzocaine 15 mg

Purpose

Oral anesthetic/Analgesic

Uses

Temporarily relieves: occasional minor irritation, pain, sore throat and sore mouth.

Warnings

Allergy Alert: Do not use this product if you have a history of allergy to local anesthetics such as procaine, butacaine, benzocaine or other “caine” anesthetics.

Sore Throat Warning: Severe or persistent sore throat or sore throat accompanied by high fever, headache, nausea, and vomiting may be serious. Consult a doctor promptly. Do not use more than 2 days or give to children under 6 years of age.

When using this product:

do not exceed recommended dosage.

Stop use and ask a dentist or doctor if:

- sore mouth symptoms do not improve in 7 days
- irritation, pain or redness persists or worsens
- swelling, rash or fever develops

If pregnant or breast-feeding,

ask a health professional before use.

Keep out of reach of children.

In case of overdose or accidental poisoning, get medical help or contact a Poison Control Center right away.

Directions

- Adults and children 6 years of age and over: Take 1 lozenge every 2 hours as needed. Allow lozenges to dissolve slowly in the mouth.
- Children under 6 years of age: contraindicated.

Other information

- Store below 25ºC.
- Protect from moisture.

Inactive ingredients

Corn syrup, Epigallocatechin Gallate (ECGC), FD&C Blue #1, FD&C Yellow #5 (tartrazine), Flavor, Honey, Propylene Glycol, Soy Lecithin, Sucrose, Glycerin, Water

PRINCIPAL DISPLAY PANEL

Chloraseptic©
Benzocaine Oral Anesthetic | Analgesic lozenges
warming
Grean Tea with real honey
18 lozenges